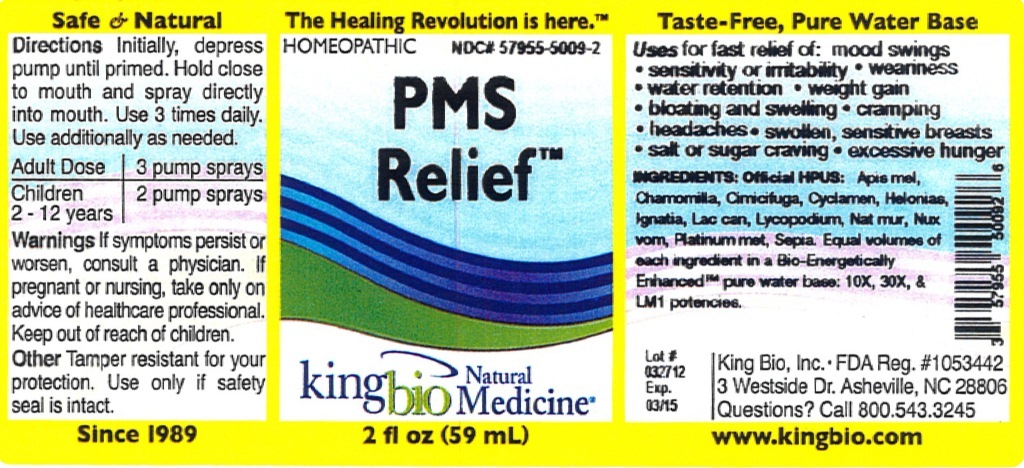 DRUG LABEL: PMS Relief
NDC: 57955-5009 | Form: LIQUID
Manufacturer: King Bio Inc.
Category: homeopathic | Type: HUMAN OTC DRUG LABEL
Date: 20120402

ACTIVE INGREDIENTS: APIS MELLIFERA 10 [hp_X]/59 mL; MATRICARIA RECUTITA 10 [hp_X]/59 mL; BLACK COHOSH 10 [hp_X]/59 mL; CYCLAMEN PURPURASCENS TUBER 10 [hp_X]/59 mL; CHAMAELIRIUM LUTEUM ROOT 10 [hp_X]/59 mL; STRYCHNOS IGNATII SEED 10 [hp_X]/59 mL; CANIS LUPUS FAMILIARIS MILK 10 [hp_X]/59 mL; LYCOPODIUM CLAVATUM SPORE 10 [hp_X]/59 mL; SODIUM CHLORIDE 10 [hp_X]/59 mL; STRYCHNOS NUX-VOMICA SEED 10 [hp_X]/59 mL; PLATINUM 10 [hp_X]/59 mL; SEPIA OFFICINALIS JUICE 10 [hp_X]/59 mL
INACTIVE INGREDIENTS: WATER

PMS Relief

Active Ingredients

Official HPUS: Apis mellifica, Chamomilla, Cimicifuga racemosa, Cyclamen europaeum, Helonias dioica, Ignatia amara, Lac caninum, Lycopodium clavatum, Natrum muriaticum, Nux vomica, Platinum metallicum, and Sepia

Reference image of pms relief.jpg

Inactive Ingredient

Equal volumes of each ingredient in a Bio-Energetically Enhanced pure water base: 10X, 30X, and LM1 potencies.

Reference image pms refief.jpg

Dosage and Administration

Directions: Hold close to mouth and spray 1 dose directly in mouth 2 to 6 times daily until symptoms improve.

Adult Dose: 3 pump sprays

Children Dose: 2-12 years 2 pump sprays

Reference image of pms relief.jpg

Purpose

For fast relief of: mood swings, sensitivity or irritability, weariness, water retention, weight gain, bloating and swelling, cramping, headaches, swollen, sensitive breast, salt or sugar craving, excessive hunger.

Reference image of pms relief.jpg

Warnings

Warnings: If symptoms persist or worsen, or if pregnant or nursing, take only on advice of a healthcare professional. Keep out of reach of children.

Other: Tamper resistant for your protection. Use only if seal is intact.

Reference image of pms relief.jpg

Keep out of reach of children.

Reference image of pms relief.jpg

Purpose

For fast relief of:

- mood swings
- sensitivity or irritability
- weariness
- water retention
- weight gain
- bloating and swelling
- cramping
- headaches
- swollen, sensitive breast
- salt or sugar craving
- excessive hunger

Reference pms relief.jpg

PACKAGE LABEL

King Bio Inc.

3 Westside Drive

Asheville, NC 28806

Questions? Call 800.543.3245

www.kingbio.com